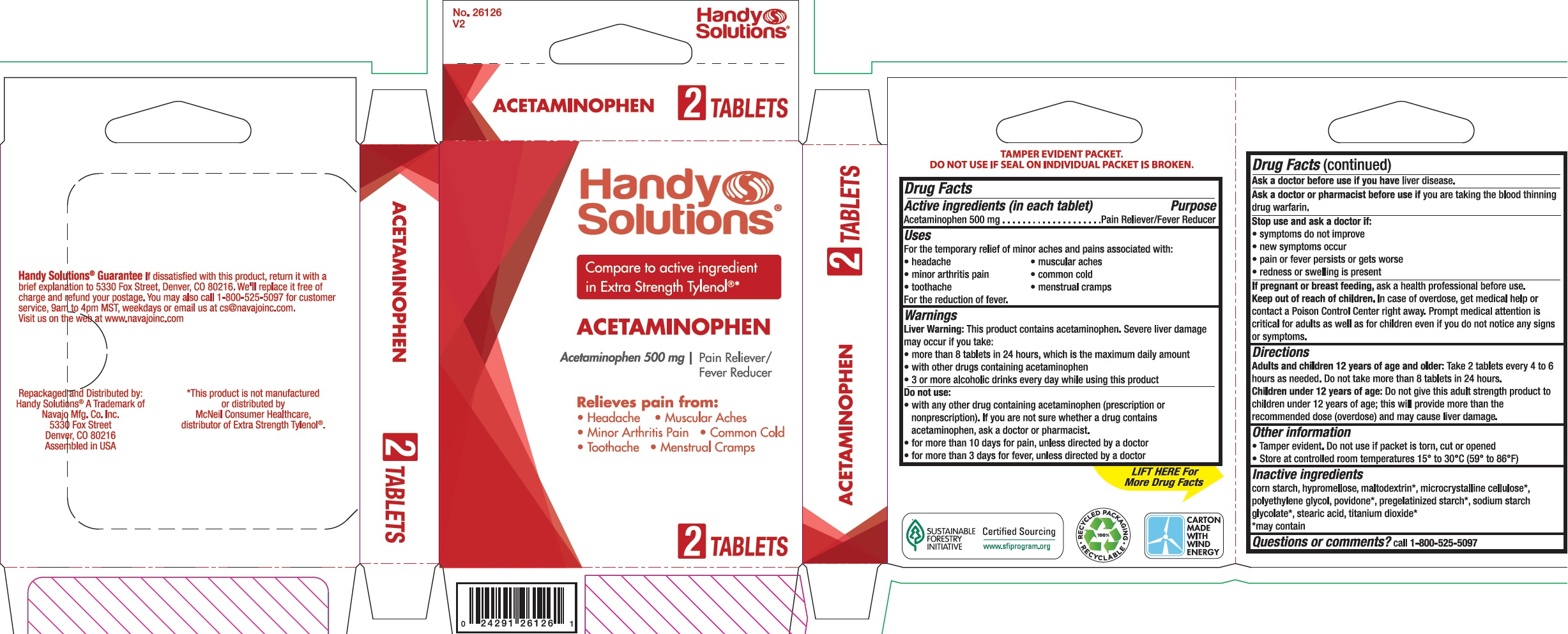 DRUG LABEL: Handy Solutions Acetaminophen
NDC: 67751-161 | Form: TABLET, FILM COATED
Manufacturer: Navajo Manufacturing Company Inc.
Category: otc | Type: HUMAN OTC DRUG LABEL
Date: 20191104

ACTIVE INGREDIENTS: ACETAMINOPHEN 500 mg/1 1
INACTIVE INGREDIENTS: STARCH, CORN; HYPROMELLOSE, UNSPECIFIED; MALTODEXTRIN; MICROCRYSTALLINE CELLULOSE; POLYETHYLENE GLYCOL, UNSPECIFIED; POVIDONE; STEARIC ACID; TITANIUM DIOXIDE

Handy Solutions Acetaminophen

Active ingredient (in each caplet)

Acetaminophen 500 mg

Purpose

Pain Reliever/Fever Reducer

Uses

For the temporary relief of minor aches and pains associated with:

• headache • muscular aches • minor arthritis pain • common cold • toothache • menstrual cramps

For the reduction of fever.

Warnings

Liver warning: This product contains acetaminophen. Severe liver damage may occur if you take:
• more than 8 tablets in 24 hours, which is the maximum daily amount
• with other drugs containing acetaminophen • 3 or more alcoholic drinks every day while using this product

Do not use

- with any other drug containing acetaminophen (prescription or nonprescription). If you are not sure whether a drug contains acetaminophen, ask a doctor or pharmacist.
- for more than 10 days for pain, unless directed by a doctor
- for more than 3 days for fever, unless directed by a doctor

Ask a doctor before use if you have

liver disease.

Ask a doctor or pharmacist before use if you are

taking the blood thinning drug warfarin.

Stop use and ask a doctor if

- symptoms do not improve
- new symptoms occur
- pain or fever persists or gets worse
- redness or swelling is present

If pregnant or breast-feeding,

ask a health professional before use.

Keep out of reach of children.

In case of overdose, get medical help or contact a Poison Control Center right away.
Prompt medical attention is critical for adults as well as for children even if you do not notice any signs or symptoms.

Directions

Adults and children 12 years of age and older: Take 2 tablets every 4 to 6 hours as needed. Do not take more than 8 tablets in 24 hours.

Children under 12 years of age: Do not give this adult strength product to children under 12 years of age; this will provide more than the recommended dose (overdose) and may cause liver damage.

Other information

- Tamper evident. Do not ues if packet is torn, cut or opened
- Store at controlled room temperatures 15° to 30° C (59 to 86°F)

Inactive ingredients

corn starch, hypromellose, maltodextrin*, microcrystalline cellulose*, polyethylene glycol, povidone*, pregelatinized starch*, sodium starch glycolate*, stearic acid, titanium dioxide*

*may contain

Questions or comments?

call 1-800-525-5097